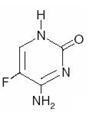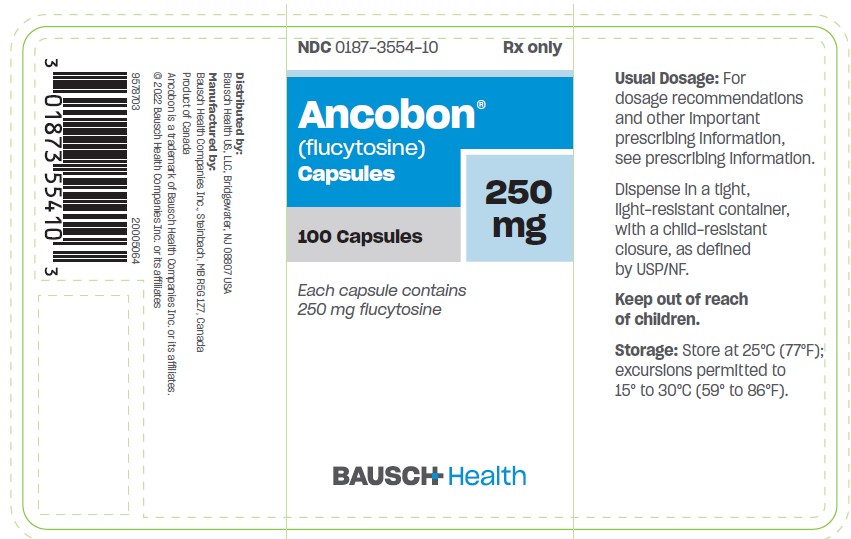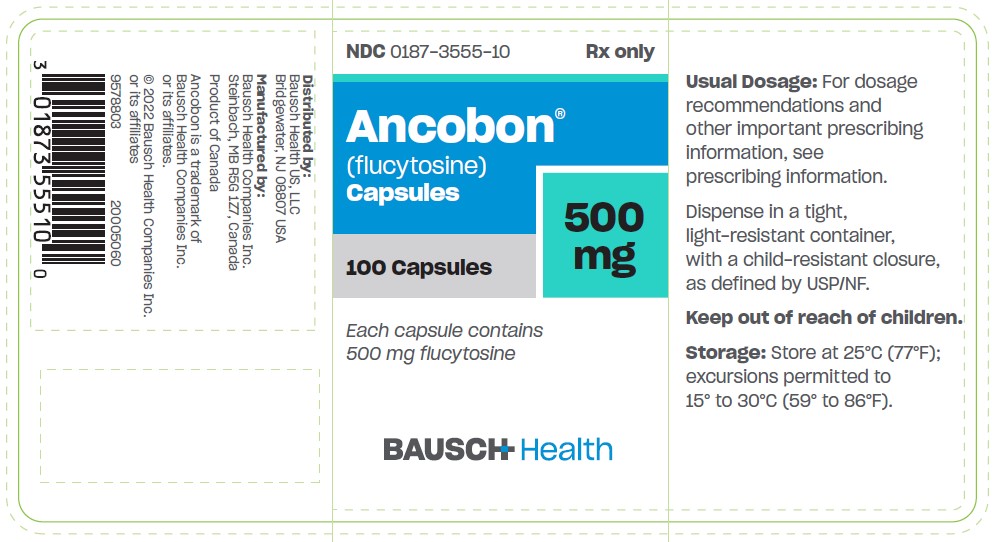 DRUG LABEL: ANCOBON
NDC: 0187-3554 | Form: CAPSULE
Manufacturer: Bausch Health US LLC
Category: prescription | Type: HUMAN PRESCRIPTION DRUG LABEL
Date: 20220202

ACTIVE INGREDIENTS: Flucytosine 250 mg/1 1
INACTIVE INGREDIENTS: STARCH, CORN; TALC; FD&C BLUE NO. 1; FD&C YELLOW NO. 6; D&C YELLOW NO. 10; TITANIUM DIOXIDE; GELATIN, UNSPECIFIED; LACTOSE, UNSPECIFIED FORM

ANCOBON®
(flucytosine)
Capsules

WARNING

Use with extreme caution in patients with impaired renal function. Close monitoring of hematologic, renal and hepatic status of all patients is essential. These instructions should be thoroughly reviewed before administration of ANCOBON.

DESCRIPTION

ANCOBON (flucytosine), an antifungal agent, is available as 250 mg and 500 mg capsules for oral administration. In addition to the active ingredient of flucytosine, each capsule contains corn starch, lactose and talc. The 250 mg capsule shell contains black iron oxide, D&C Yellow No. 10, FD&C Blue No. 1, FD&C Yellow No. 6, gelatin and titanium dioxide. The 500 mg capsule shell contains black iron oxide, gelatin and titanium dioxide.

Chemically, flucytosine is 5-fluorocytosine, a fluorinated pyrimidine which is related to fluorouracil and floxuridine. It is a white to off-white crystalline powder with a molecular weight of 129.09 and the following structural formula:

CLINICAL PHARMACOLOGY

Flucytosine is rapidly and virtually completely absorbed following oral administration. ANCOBON is not metabolized significantly when given orally to man. Bioavailability estimated by comparing the area under the curve of serum concentrations after oral and intravenous administration showed 78% to 89% absorption of the oral dose. Peak serum concentrations of 30 to 40 mcg/mL were reached within 2 hours of administration of a 2 g oral dose to normal subjects. Other studies revealed mean serum concentrations of approximately 70 to 80 mcg/mL 1 to 2 hours after a dose in patients with normal renal function receiving a 6-week regimen of flucytosine (150 mg/kg/day given in divided doses every 6 hours) in combination with amphotericin B. The half-life in the majority of healthy subjects ranged between 2.4 and 4.8 hours. Flucytosine is excreted via the kidneys by means of glomerular filtration without significant tubular reabsorption. More than 90% of the total radioactivity after oral administration was recovered in the urine as intact drug. Flucytosine is deaminated (probably by gut bacteria) to 5-fluorouracil. The area under the curve (AUC) ratio of 5-fluorouracil to flucytosine is 4%. Approximately 1% of the dose is present in the urine as the α-fluoro-β-ureido-propionic acid metabolite. A small portion of the dose is excreted in the feces.

The half-life of flucytosine is prolonged in patients with renal insufficiency; the average half-life in nephrectomized or anuric patients was 85 hours (range: 29.9 to 250 hours). A linear correlation was found between the elimination rate constant of flucytosine and creatinine clearance.

In vitro studies have shown that 2.9% to 4% of flucytosine is protein-bound over the range of therapeutic concentrations found in the blood. Flucytosine readily penetrates the blood-brain barrier, achieving clinically significant concentrations in cerebrospinal fluid.

Pharmacokinetics in Pediatric Patients

Limited data are available regarding the pharmacokinetics of ANCOBON administered to neonatal patients being treated for systemic candidiasis. After five days of continuous therapy, median peak levels in infants were 19.6 mcg/mL, 27.7 mcg/mL, and 83.9 mcg/mL at doses of 25 mg/kg (N=3), 50 mg/kg (N=4), and 100 mg/kg (N=3), respectively. Mean time to peak serum levels was of 2.5 ± 1.3 hours, similar to that observed in adult patients. A good deal of interindividual variability was noted, which did not correlate with gestational age. Some patients had serum levels > 100 mcg/mL, suggesting a need for drug level monitoring during therapy. In another study, serum concentrations were determined during flucytosine therapy in two patients (total assays performed =10). Median serum flucytosine concentrations at steady state were calculated to be 57 ± 10 mcg/mL (doses of 50 to 125 mg/kg/day, normalized to 25 mg/kg per dose for comparison). In three infants receiving flucytosine 25 mg/kg/day (four divided doses), a median flucytosine half-life of 7.4 hours was observed, approximately double that seen in adult patients. The concentration of flucytosine in the cerebrospinal fluid of one infant was 43 mcg/mL 3 hours after a 25 mg oral dose, and ranged from 20 to 67 mg/L in another neonate receiving oral doses of 120 to 150 mg/kg/day.

MICROBIOLOGY

Mechanism of Action

Flucytosine is taken up by fungal organisms via the enzyme cytosine permease. Inside the fungal cell, flucytosine is rapidly converted to fluorouracil by the enzyme cytosine deaminase. Fluorouracil exerts its antifungal activity through the subsequent conversion into several active metabolites, which inhibit protein synthesis by being falsely incorporated into fungal RNA or interfere with the biosynthesis of fungal DNA through the inhibition of the enzyme thymidylate synthetase.

Activity In Vitro

Flucytosine has been shown to be active against most strains of the following microorganisms both in vitro and in clinical infections.

Candida albicans

Cryptococcus neoformans

Susceptibility Testing

For specific information regarding susceptibility test interpretive criteria and associated test methods and quality control standards recognized by FDA for this drug, please see: https://www.fda.gov/STIC.

Drug Resistance

Flucytosine resistance may arise from a mutation of an enzyme necessary for the cellular uptake or metabolism of flucytosine or from an increased synthesis of pyrimidines, which compete with the active metabolites of flucytosine (fluorinated antimetabolites). Resistance to flucytosine has been shown to develop during monotherapy after prolonged exposure to the drug.

Drug Combination

Antifungal synergism between flucytosine and polyene antibiotics, particularly amphotericin B has been reported in vitro. ANCOBON is usually administered in combination with amphotericin B due to lack of cross-resistance and reported synergistic activity of both drugs.

INDICATIONS AND USAGE

ANCOBON is indicated only in the treatment of serious infections caused by susceptible strains of Candida and/or Cryptococcus.

Candida: Septicemia, endocarditis and urinary system infections have been effectively treated with flucytosine. Limited trials in pulmonary infections justify the use of flucytosine.

Cryptococcus: Meningitis and pulmonary infections have been treated effectively. Studies in septicemias and urinary tract infections are limited, but good responses have been reported.

ANCOBON should be used in combination with amphotericin B for the treatment of systemic candidiasis and cryptococcosis because of the emergence of resistance to ANCOBON (see MICROBIOLOGY).

CONTRAINDICATIONS

ANCOBON is contraindicated in patients with a known hypersensitivity to the drug.

ANCOBON is contraindicated in patients with known complete dihydropyrimidine dehydrogenase (DPD) enzyme deficiency (see WARNINGS).

WARNINGS

ANCOBON must be given with extreme caution to patients with impaired renal function. Since ANCOBON is excreted primarily by the kidneys, renal impairment may lead to accumulation of the drug. ANCOBON serum concentrations should be monitored to determine the adequacy of renal excretion in such patients. Dosage adjustments should be made in patients with renal insufficiency to prevent progressive accumulation of active drug.

ANCOBON must be given with extreme caution to patients with bone marrow depression. Patients may be more prone to depression of bone marrow function if they: 1) have a hematologic disease, 2) are being treated with radiation or drugs which depress bone marrow, or 3) have a history of treatment with such drugs or radiation. Bone marrow toxicity can be irreversible and may lead to death in immunosuppressed patients. Frequent monitoring of hepatic function and of the hematopoietic system is indicated during therapy.

5-Fluorouracil is a metabolite of flucytosine. Dihydropyrimidine dehydrogenase is a key enzyme involved in the metabolism and elimination of 5-fluorouracil. Therefore, the risk of severe drug toxicity is increased when ANCOBON is used in individuals with deficiency in DPD. Possible drug toxicities include mucositis, diarrhea, neutropenia, and neurotoxicity. Determination of DPD activity may be considered where drug toxicity is confirmed or suspected. In the event of suspected drug toxicity, consider stopping ANCOBON treatment.

PRECAUTIONS

General

Before therapy with ANCOBON is instituted, electrolytes (because of hypokalemia) and the hematologic and renal status of the patient should be determined (see WARNINGS). Close monitoring of the patient during therapy is essential.

Laboratory Tests

Since renal impairment can cause progressive accumulation of the drug, blood concentrations and kidney function should be monitored during therapy. Hematologic status (leukocyte and thrombocyte count) and liver function (alkaline phosphatase, SGOT and SGPT) should be determined at frequent intervals during treatment as indicated.

Drug Interactions

Cytosine arabinoside, a cytostatic agent, has been reported to inactivate the antifungal activity of ANCOBON by competitive inhibition. Drugs which impair glomerular filtration may prolong the biological half-life of flucytosine.

Drug/Laboratory Test Interactions

Measurement of serum creatinine levels should be determined by the Jaffé reaction, since ANCOBON does not interfere with the determination of creatinine values by this method. Most automated equipment for measurement of creatinine makes use of the Jaffé reaction.

Carcinogenesis, Mutagenesis, Impairment of Fertility

Flucytosine has not undergone adequate animal testing to evaluate carcinogenic potential. The mutagenic potential of flucytosine was evaluated in Ames-type studies with five different mutants of S. typhimurium and no mutagenicity was detected in the presence or absence of activating enzymes. Flucytosine was nonmutagenic in three different repair assay systems (i.e., rec, uvr and pol).

There have been no adequate trials in animals on the effects of flucytosine on fertility or reproductive performance. The fertility and reproductive performance of the offspring (F1 generation) of mice treated with 100 mg/kg/day (345 mg/M^2/day or 0.059 times the human dose), 200 mg/kg/day (690 mg/M^2/day or 0.118 times the human dose) or 400 mg/kg/day (1380 mg/M^2/day or 0.236 times the human dose) of flucytosine on days 7 to 13 of gestation was studied; the in utero treatment had no adverse effect on the fertility or reproductive performance of the offspring.

Pregnancy

Teratogenic Effects

Flucytosine was shown to be teratogenic (vertebral fusions) in the rat at doses of 40 mg/kg/day (298 mg/M^2/day or 0.051 times the human dose) administered on days 7 to 13 of gestation. At higher doses (700 mg/kg/day; 5208 mg/M^2/day or 0.89 times the human dose administered on days 9 to 12 of gestation), cleft lip and palate and micrognathia were reported. Flucytosine was not teratogenic in rabbits up to a dose of 100 mg/kg/day (1423 mg/M^2/day or 0.243 times the human dose) administered on days 6 to 18 of gestation. In mice, 400 mg/kg/day of flucytosine (1380 mg/M^2/day or 0.236 times the human dose) administered on days 7 to 13 of gestation was associated with a low incidence of cleft palate that was not statistically significant. Studies in pregnant rats have shown that flucytosine injected intraperitoneally crosses the placental barrier. There are no adequate and well-controlled studies in pregnant women. ANCOBON should be used during pregnancy only if the potential benefit justifies the potential risk to the fetus.

Nursing Mothers

It is not known whether this drug is excreted in human milk. Because many drugs are excreted in human milk and because of the potential for serious adverse reactions in nursing infants from ANCOBON, a decision should be made whether to discontinue nursing or to discontinue the drug, taking into account the importance of the drug to the mother.

Pediatric Use

The efficacy and safety of ANCOBON have not been systematically studied in pediatric patients. A small number of neonates have been treated with 25 to 200 mg/kg/day of flucytosine, with and without the addition of amphotericin B, for systemic candidiasis. No unexpected adverse reactions were reported in these patients. It should be noted, however, that hypokalemia and acidemia were reported in one patient who received flucytosine in combination with amphotericin B, and anemia was observed in a second patient who received flucytosine alone. Transient thrombocytopenia was noted in two additional patients, one of whom also received amphotericin B.

ADVERSE REACTIONS

The adverse reactions which have occurred during treatment with ANCOBON are grouped according to organ system affected.

Cardiovascular: Cardiac arrest, myocardial toxicity, ventricular dysfunction.

Respiratory: Respiratory arrest, chest pain, dyspnea.

Dermatologic: Rash, pruritus, urticaria, photosensitivity.

Gastrointestinal: Nausea, emesis, abdominal pain, diarrhea, anorexia, dry mouth, duodenal ulcer, gastrointestinal hemorrhage, acute hepatic injury including hepatic necrosis with possible fatal outcome in debilitated patients, hepatic dysfunction, jaundice, ulcerative colitis, enterocolitis, bilirubin elevation, increased hepatic enzymes.

Genitourinary: Azotemia, creatinine and BUN elevation, crystalluria, renal failure.

Hematologic: Anemia, agranulocytosis, aplastic anemia, eosinophilia, leukopenia, pancytopenia, thrombocytopenia, and fatal cases of bone marrow aplasia.

Neurologic: Ataxia, hearing loss, headache, paresthesia, parkinsonism, peripheral neuropathy, pyrexia, vertigo, sedation, convulsions.

Psychiatric: Confusion, hallucinations, psychosis.

Miscellaneous: Fatigue, hypoglycemia, hypokalemia, weakness, allergic reactions, Lyell’s syndrome.

To report SUSPECTED ADVERSE REACTIONS, contact Bausch Health US, LLC at 1-800-321-4576 or FDA at 1-800-FDA-1088 or www.fda.gov/medwatch.

OVERDOSAGE

There is no experience with intentional overdosage. It is reasonable to expect that overdosage may produce pronounced manifestations of the known clinical adverse reactions. Prolonged serum concentrations in excess of 100 mcg/mL may be associated with an increased incidence of toxicity, especially gastrointestinal (diarrhea, nausea, vomiting), hematologic (leukopenia, thrombocytopenia) and hepatic (hepatitis).

In the management of overdosage, prompt gastric lavage or the use of an emetic is recommended. Adequate fluid intake should be maintained, by the intravenous route if necessary, since ANCOBON is excreted unchanged via the renal tract. The hematologic parameters should be monitored frequently; liver and kidney function should be carefully monitored. Should any abnormalities appear in any of these parameters, appropriate therapeutic measures should be instituted.

Since hemodialysis has been shown to rapidly reduce serum concentrations in anuric patients, this method may be considered in the management of overdosage.

DOSAGE AND ADMINISTRATION

The usual dosage of ANCOBON is 50 to 150 mg/kg/day administered in divided doses at 6-hour intervals. Nausea or vomiting may be reduced or avoided if the capsules are given a few at a time over a 15-minute period. If the BUN or the serum creatinine is elevated, or if there are other signs of renal impairment, the initial dose should be at the lower level (see WARNINGS).

ANCOBON should be used in combination with amphotericin B for the treatment of systemic candidiasis and cryptococcosis because of the emergence of resistance to ANCOBON (see MICROBIOLOGY).

HOW SUPPLIED ANCOBON® (flucytosine) Capsules are supplied as capsules containing 250 mg and 500 mg flucytosine as follows:

NDC | Strength | Package Configuration | Description
0187‑3554‑10 | 250 mg | Bottles of 100 | Gray and green capsules imprinted with “ANCOBON® 250 ICN”
0187‑3555‑10 | 500 mg | Bottles of 100 | Gray and white capsules imprinted with “ANCOBON® 500 ICN”

Store at 25°C (77°F); excursions permitted to 15° to 30°C (59° to 86°F).

Distributed by:

Bausch Health US, LLC

Bridgewater, NJ 08807 USA

Manufactured by:

Bausch Health Companies Inc.

Steinbach, MB R5G 1Z7, Canada

ANCOBON is a trademark of Bausch Health Companies Inc. or its affiliates.

© 2022 Bausch Health Companies Inc. or its affiliates

Rev. 02/2022
9578603
20005061

PRINCIPAL DISPLAY PANEL - 250 mg Capsule Bottle Label

NDC 0187-3554-10
Rx only

Ancobon®
(flucytosine)
Capsules

250 mg

100 Capsules

Each capsule contains
250 mg flucytosine

BAUSCH Health

9578703
20005064

PRINCIPAL DISPLAY PANEL - 500 mg Capsule Bottle Label

NDC 0187-3555-10
Rx only

Ancobon®
(flucytosine)
Capsules

500 mg

100 Capsules

Each capsule contains
500 mg flucytosine

BAUSCH Health

9578803
20005060